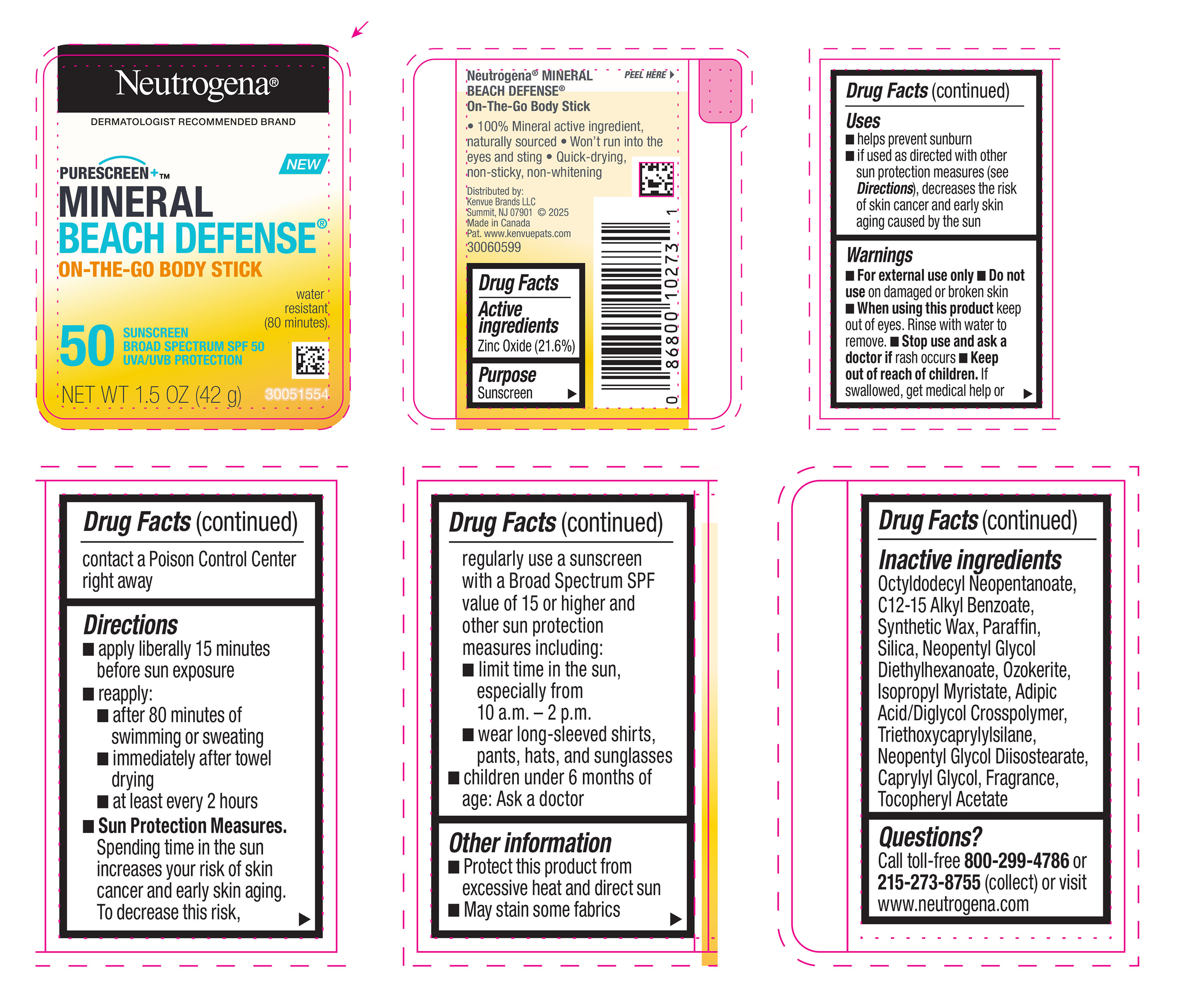 DRUG LABEL: Neutrogena Mineral Beach Defense On-The-Go Body SPF 50
NDC: 69968-0775 | Form: STICK
Manufacturer: Kenvue Brands LLC
Category: otc | Type: HUMAN OTC DRUG LABEL
Date: 20250710

ACTIVE INGREDIENTS: ZINC OXIDE 216 mg/1 g
INACTIVE INGREDIENTS: ADIPIC ACID/DIGLYCOL CROSSPOLYMER (20000 MPA.S); TRIETHOXYCAPRYLYLSILANE; NEOPENTYL GLYCOL DIISOSTEARATE; CAPRYLYL GLYCOL; ALPHA-TOCOPHEROL ACETATE; ALKYL (C12-15) BENZOATE; PARAFFIN; SILICON DIOXIDE; NEOPENTYL GLYCOL DIETHYLHEXANOATE; CERESIN; ISOPROPYL MYRISTATE; OCTYLDODECYL NEOPENTANOATE

Neutrogena Mineral Beach Defense On-The-Go Body Stick SPF 50

Drug Facts

Active ingredients | Purpose
Zinc Oxide (21.6%) | Sunscreen

Purpose

Sunscreen

Uses

- helps prevent sunburn
- if used as directed with other sun protection measures (see Directions), decreases the risk of skin cancer and early skin aging caused by the sun

Warnings

For external use only

Do not use on damaged or broken skin

When using this product keep out of eyes. Rinse with water to remove.

Stop use and ask a doctor if rash occurs

Keep out of reach of children. If swallowed, get medical help or contact a Poison Control Center right away

Directions

- apply liberally 15 minutes before sun exposure
- reapply:
- after 80 minutes of swimming or sweating
- immediately after towel drying
- at least every 2 hours
- Sun Protection Measures. Spending time in the sun increases your risk of skin cancer and early skin aging. To decrease this risk, regularly use a sunscreen with a Broad Spectrum SPF value of 15 or higher and other sun protection measures including:
- limit time in the sun, especially from 10 a.m. – 2 p.m.
- wear long-sleeved shirts, pants, hats, and sunglasses
- children under 6 months of age: Ask a doctor

Other information

- Protect this product from excessive heat and direct sun
- May stain some fabrics

Inactive ingredients

Octyldodecyl Neopentanoate, C12-15 Alkyl Benzoate, Synthetic Wax, Paraffin, Silica, Neopentyl Glycol Diethylhexanoate, Ozokerite, Isopropyl Myristate, Adipic Acid/Diglycol Crosspolymer, Triethoxycaprylylsilane, Neopentyl Glycol Diisostearate, Caprylyl Glycol, Fragrance, Tocopheryl Acetate

Questions?

Call toll-free 800-299-4786 or 215-273-8755 (collect) or visit www.neutrogena.com

Distributed by:

Kenvue Brands LLC
Summit, NJ 07901

PRINCIPAL DISPLAY PANEL - 42 g Canister

Neutrogena®

DERMATOLOGIST RECOMMENDED BRAND

NEW

PURESCREEN+TM

MINERAL

BEACH DEFENSE®

ON-THE-GO BODY STICK

water

resistant

(80 minutes)

50

SUNSCREEN

BROAD SPECTRUM SPF 50

UVA/UVB PROTECTION

NET WT 1.5 OZ (42 g)